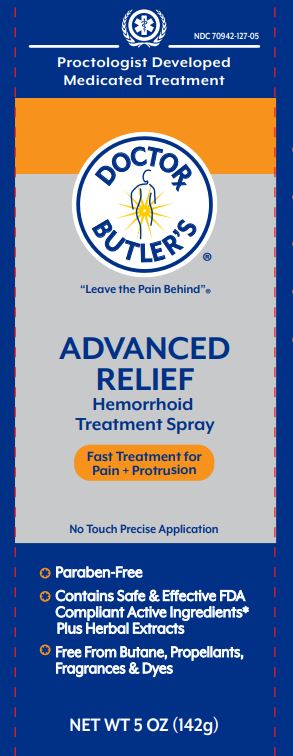 DRUG LABEL: Dr Butlers Advanced Hemorrhoid Relief
NDC: 70942-127 | Form: SPRAY
Manufacturer: Beyond Health. PA
Category: otc | Type: HUMAN OTC DRUG LABEL
Date: 20250723

ACTIVE INGREDIENTS: WITCH HAZEL 50 g/100 g; LIDOCAINE HCL 5 g/100 g; PHENYLEPHRINE HYDROCHLORIDE 0.25 g/100 g
INACTIVE INGREDIENTS: CALENDULA OFFICINALIS FLOWER; EPILOBIUM ANGUSTIFOLIUM LEAF; OLEA EUROPAEA (OLIVE) LEAF; ASIAN GINSENG; ROSEMARY; CHAMOMILE; EUCALYPTUS OIL; POLYSORBATE 40; TOCOPHEROL; CARYA OVATA BARK; HORSE CHESTNUT; MELALEUCA ALTERNIFOLIA LEAF; PROPYLENE GLYCOL; HAMAMELIS VIRGINIANA LEAF; HYALURONATE SODIUM; CENTELLA ASIATICA LEAF; ALCOHOL; BENZYL ALCOHOL; ETHYLHEXYLGLYCERIN; TURMERIC; LYSINE HCL; WATER; ALOE VERA LEAF; BENZOPHENONE-4; HELICHRYSUM ITALICUM FLOWER; PEPPERMINT OIL; ALPHA-TOCOPHEROL ACETATE; SODIUM CITRATE; HYDROXYETHYLCELLULOSE; LAVANDULA ANGUSTIFOLIA (LAVENDER) FLOWER; GLYCERIN; EDETATE DISODIUM

Doctor Butler's Advanced Hemorrhoid Relief Spray

Active Ingredients

Lidocaine HCl 5%

Phenylephrine HCl 0.25%

Witch Hazel 50%

Purpose

External Analgesic

Vasoconstrictor

Astrigent

Uses

- temporary relief of anorectal itching and discomfort associated with hemorrhoids and other anorectal disorders
- for the temporary relief of pain, soreness or burning
- temporarily reduces the swelling associated with hemorrhoids
- temporarily shrinks hemorrhoidal tissue

Warnings

For external use only.

Flammable

Do not use whie smoking or near heat or flame.

Do not use

in large quantities, particularly over raw surfaces or blistered areas. Do not exceed recommended dosage unless directed by a doctor.

When using this product

- keep out of eyes. Rinse eyes with water to remove
- do not put this product in the rectum by using fingers or any mechanical device or applicator

Ask a doctor or pharmacist before use if you have

- heart disease, high blood pressure, thyroid disease, diabetes, difficulty in urination due to enlargement of the prostate gland
- are presently taking a prescription drug for high blood pressure or depression

Stop use and ask a doctor if

- condition worsens or does not improve within seven (7) days
- bleeding occurs
- an allergic reaction develops
- the symptom being treated does not subside or if redness, irritation, swelling, pain or other symptoms develop or icrease

If pregnant or breastfeeding

ask a health professioal before use.

Keep out of reach of children.

If swallowed, get medical help or contact a Poison Control Center right away.

Directions

- adults, when practical, cleanse the affected area by pattig or blotting with an appropriate cleansing pad
- gently dry by patting or blotting with toie tissue or soft cloth before application of this product
- shake well before using
- hold 3 to 6" away from rectal area, spray to moisten and then wipe off excess, if desired
- apply externally to the affected area up to 4 times daily
- chidren under 12 years of age, consult a doctor

Other Information

- store at 15º-30ºC (59º-86ºF)
- contents under pressure. Do not puncture or incinerate

Inactive ingredients

aesculus hippocastanum (horse chestnut) extract

alcohol

aloe barbadensis leaf extract

benzophenone-4

benzyl alcohol

calendula officinalis flower extract

carya ovata bark extract

centella asiatica extract

chamomilla recutita (matricaria) flower extract

curcuma longa (tumeric) root extract

disodium EDTA

epilobium angustifolium extract

ethylhexylglycerin

eucalyptus globulus leaf oil

glycerin

hammamelis virginiana (witch hazel) leaf extract

helichrysum italicum extract

hydroxyethylcellulose

lavandula angustifolia (lavender) flower extract

lysine HCl

melaluca alternifolia (tea tree) leaf extract

mentha piperita (peppermint) oil

olea europaea (olive) leaf extract

panax ginsing root extract

polysorbate 40

propylene glycol

rosmarinus officinalis (rosemary) leaf extract

sodium citrate

sodium hyaluronate

tocopherol

tocopherol acetate

water